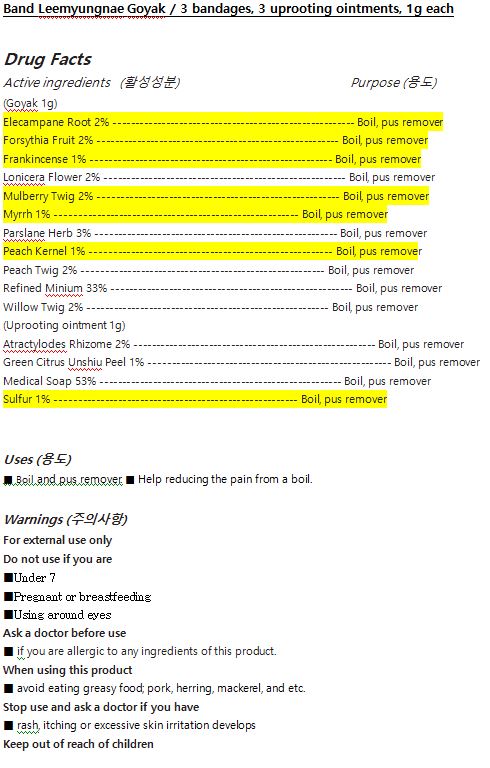 DRUG LABEL: Band Leemyungnae Goyak
NDC: 72850-0006 | Form: OINTMENT
Manufacturer: Chunwoo Pharmaceutical Co., Ltd.
Category: otc | Type: HUMAN OTC DRUG LABEL
Date: 20200116

ACTIVE INGREDIENTS: ATRACTYLODES LANCEA ROOT 2 g/100 g; CITRUS AURANTIUM FRUIT 1 g/100 g; PRUNUS PERSICA LEAF 2 g/100 g; CHENOPODIUM ALBUM WHOLE 52 g/100 g; SALIX ALBA BARK 2 g/100 g; MORUS ALBA STEM 2 g/100 g; FRANKINCENSE 1 g/100 g; INULA HELENIUM ROOT 2 g/100 g; FORSYTHIA SUSPENSA FRUIT 2 g/100 g; MYRRH 1 g/100 g; PRUNUS PERSICA SEED 1 g/100 g; SULFUR 1 g/100 g; LONICERA DASYSTYLA FLOWER BUD 2 g/100 g; PURSLANE 3 g/100 g; LEAD TETROXIDE 33 g/100 g
INACTIVE INGREDIENTS: SUCROSE; RICE OIL

Drug Facts

ACTIVE INGREDIENT

(Goyak 1g)

Aucklandiae Radix 2% --------------------------------------------------------------- Boil, pus remover

Forsythia Fruit 2% -------------------------------------------------------------------- Boil, pus remover

Frankincense 1% --------------------------------------------------------------------- Boil, pus remover

Lonicera 2% -------------------------------------------------------------------------- Boil, pus remover

Mulberry Twig 2% ------------------------------------------------------------------- Boil, pus remover

Myrrh 1% ----------------------------------------------------------------------------- Boil, pus remover

Purslane Herb 3% -------------------------------------------------------------------- Boil, pus remover

Peach Seed 1% ---------------------------------------------------------------------- Boil, pus remover

Peach Leaf 2% ----------------------------------------------------------------------- Boil, pus remover

Minium 33% ------------------------------------------------------------------------- Boil, pus remover

Salix Alba Bark 2% ------------------------------------------------------------------- Boil, pus remover

(Uprooting ointment 1g)

Atractylodes Rhizome 2% ----------------------------------------------------------- Boil, pus remover

Citrus Aurantium Fruit, Immature 1% ----------------------------------------------- Boil, pus remover

Sulfur 1% ----------------------------------------------------------------------------- Boil, pus remover

Chenopodium Album Whole 52% -------------------------------------------------- Boil, pus remover

INACTIVE INGREDIENT

- Goyak

Rice Oil, Bandage

- Uprooting Ointment

Rice Oil, Sucrose

PURPOSE

■ Boil and pus remover. ■ Help reducing the pain from a boil

keep out of reach of the children

INDICATIONS AND USAGE

■ Wash your hands and clean affected area

■ before a boil or a pus is festering, attach the plaster only to cover the affected area.

■ when a boil or a pus festering, insert an uprooting ointment into the area and attach the plaster on it.

■ Change to a new plaster after a day or two while symptom persists.

WARNINGS

For external use only
Do not use if you are

■Under 7

■Pregnant or breastfeeding

■Using around eyes

Ask a doctor before use

■ if you are allergic to any ingredients of this product.

When using this product

■ avoid eating greasy food; pork, herring, mackerel, and etc.

Stop use and ask a doctor if you have

■ rash, itching or excessive skin irritation develops

DOSAGE AND ADMINISTRATION

for external use only